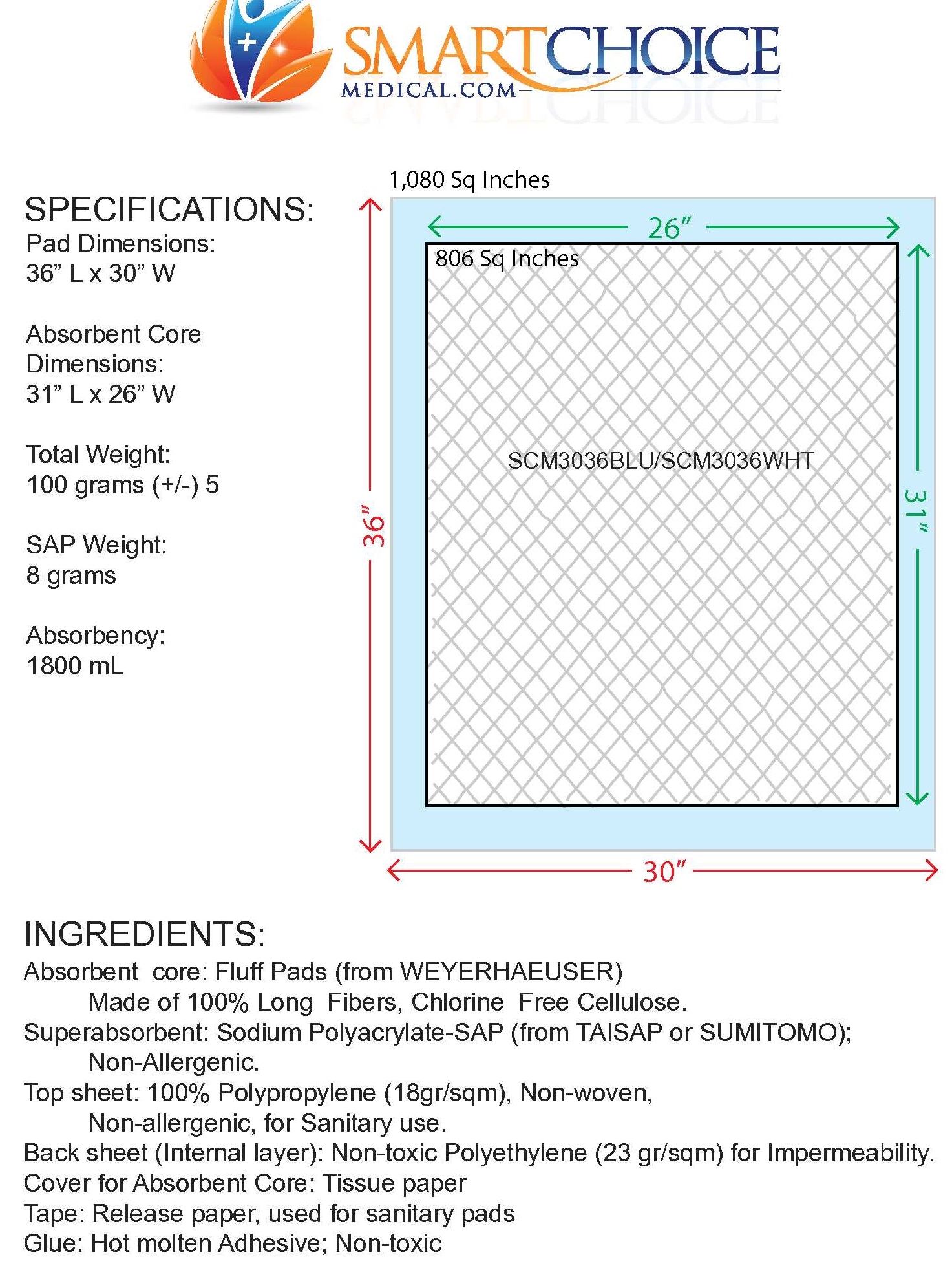 DRUG LABEL: HEXASORB UNDERPADS
NDC: 70936-202
Manufacturer: SMART CHOICE MEDICAL INC.
Category: other | Type: MEDICAL DEVICE
Date: 20180119

HEXASORB UNDERPADS